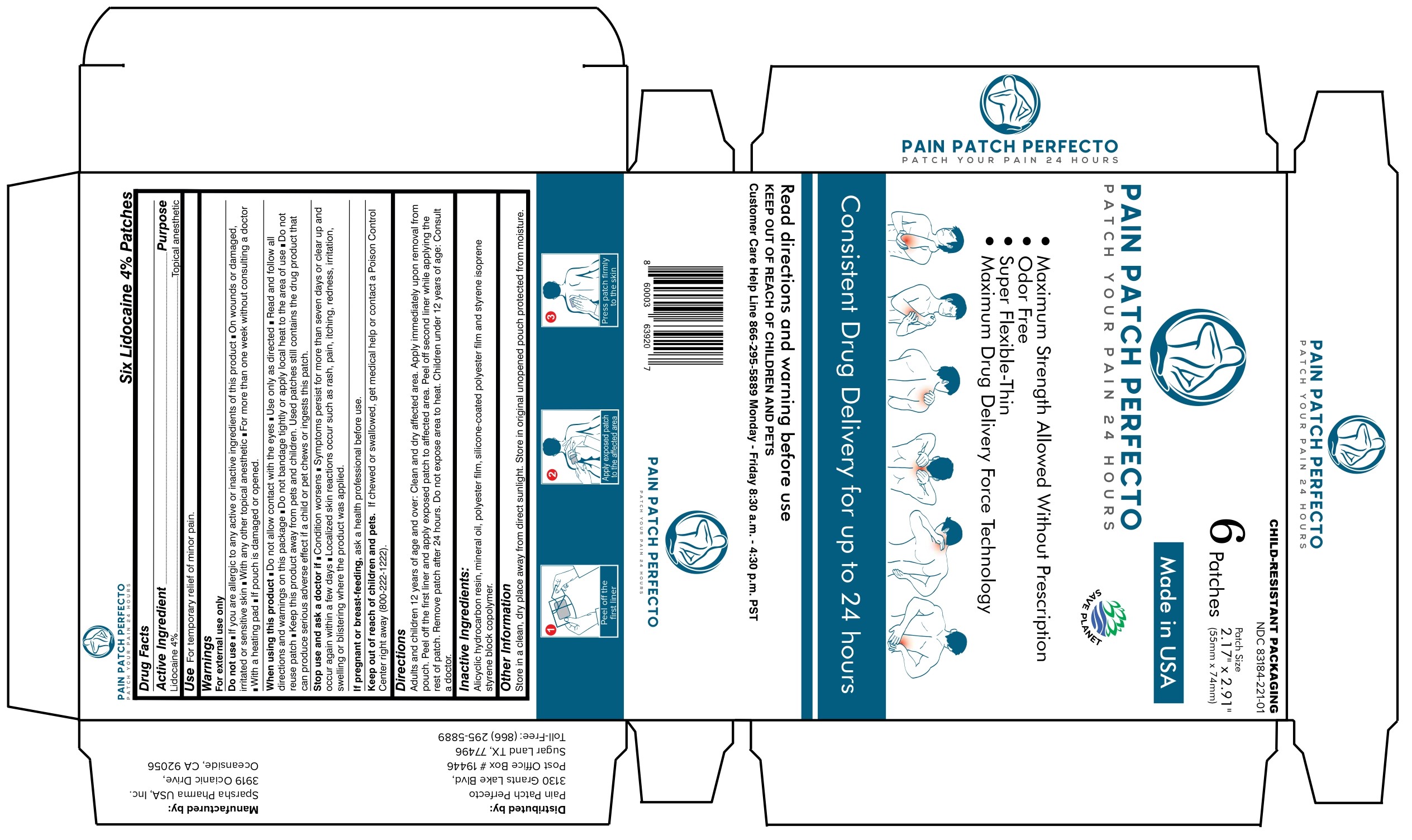 DRUG LABEL: Pain Patch Perfecto 24 Hours Lidocaine 4 % Patch
NDC: 83184-221 | Form: PATCH
Manufacturer: Painpatchperfecto LLC
Category: otc | Type: HUMAN OTC DRUG LABEL
Date: 20251225

ACTIVE INGREDIENTS: LIDOCAINE 4 g/100 g
INACTIVE INGREDIENTS: MINERAL OIL; HYDROGENATED C6-20 POLYOLEFIN (100 CST); STYRENE/ISOPRENE/STYRENE BLOCK COPOLYMER (STYRENE/ISOPRENE 15/85)

PAIN PATCH PERFECTO 24 HOURS LIDOCAINE 4% PATCH

Active Ingredient

Lidocaine 4%

Purpose

Topical anesthetic

Use

For the temporary relief of minor pain.

Warnings

For External Use Only

Do not use

• If you are allergic to any active or inactive ingredients of this product
• On wounds or damaged, irritated or sensitive skin
• With any other topical anesthetic
• For more than one week without consulting a doctor
• With a heating pad
• If pouch is damaged or opened.

When using this product

• Do not allow contact with the eyes
• Use only as directed
• Read and follow all directions and warnings on this package
• Do not bandage tightly or apply local heat to the area of use
• Do not reuse patch
• Keep this product away from pets and children. Used patches still contains the drug product that can produce serious adverse effect if child or pet chews or ingest this patch.

Stop use and ask a doctor if

• Condition worsens
• Symptoms persist for more than seven days or clear up and occur again within a few days
• Localized skin reactions occur such as rash, pain, itching, redness, irritation, swelling or blistering where the product was applied.

PREGNANCY OR BREAST FEEDING

If pregnant or breast-feeding, ask a health professional before use.

Keep out of reach of children and pets. If chewed or swallowed, get medical help or contact a Poison Control Center right away (800-222-1222).

Directions

Adults and children 12 years of age and over: Clean and dry affected area. Apply immediately upon removal from pouch. Peel off the first liner and apply exposed patch to affected area. Peel off second liner while applying the rest of patch. Remove patch after 24 hours. Do not expose area to heat.

Children under 12 years of age: Consult a doctor.

Inactive Ingredients

Alicyclic hydrocarbon resin, mineral oil, polyester film, silicon-coated polyester film and styrene isoprene styrene block copolymer.

Other information

Store in a clean, dry place away from direct sunlight. Store in original unopened pouch. protected from moisture.

Questions ?

Customer Care Help Line 866-295-5889 Monday - Friday 8:30 a.m. - 4:30 p.m. PST